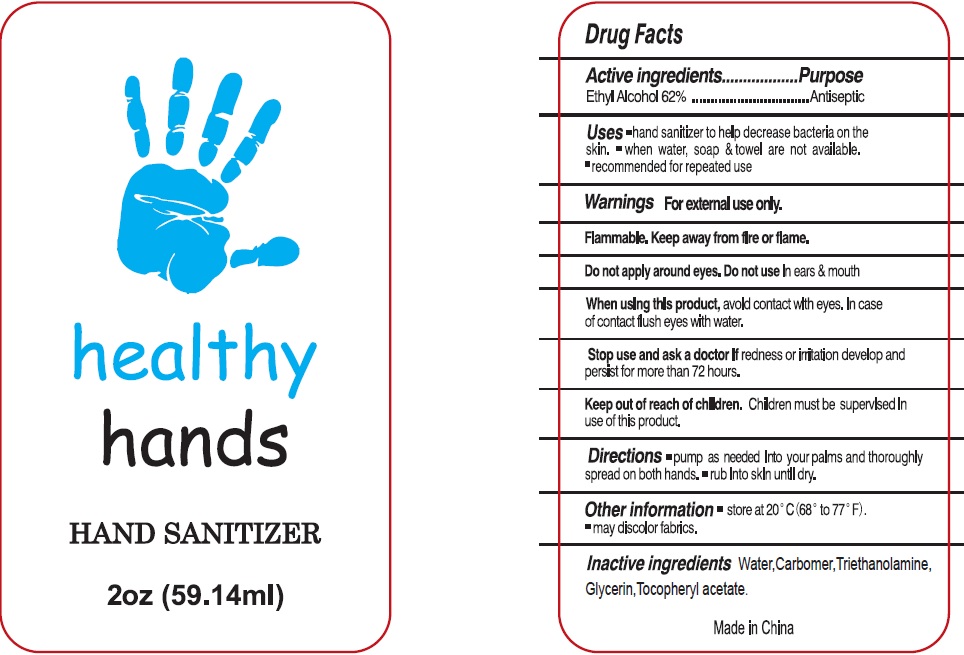 DRUG LABEL: Hand Sanitizer
NDC: 73260-010 | Form: GEL
Manufacturer: Yuyao YiJia Daily Chemical Co., Ltd.
Category: otc | Type: HUMAN OTC DRUG LABEL
Date: 20200511

ACTIVE INGREDIENTS: ALCOHOL 0.62 mL/1 mL
INACTIVE INGREDIENTS: WATER; CARBOMER HOMOPOLYMER, UNSPECIFIED TYPE; TROLAMINE; GLYCERIN; .ALPHA.-TOCOPHEROL ACETATE

Hand Sanitizer

Active ingredients

Ethyl Alcohol 62%

Purpose

Antiseptic

Uses

- hand sanitizer to help decrease bacteria on the skin.
- when water, soap & towel are not available.
- recommended for repeated use

Warnings

For external use only. Flammable. Keep away from heat or flame.

Do not apply around eyes.

Do not use

In ears & mouth

When using this product

avoid contact with eyes, In case of contact flush eyes with water.

Stop use and ask a doctor

If redness or irritation develop and persist for more than 72 hours.

Keep out of reach of children.

Children must be supervised in use of this product.

Directions

- pump as needed into your palms and thoroughly spread on both hands.
- rub into skin until dry.

Other information

- store at 20°C (68° to 77°F).
- may discolor fabrics.

Inactive ingredients:

Purified water, Carbomer, Triethanolamine, Glycerin, Tocopheryl acetate.